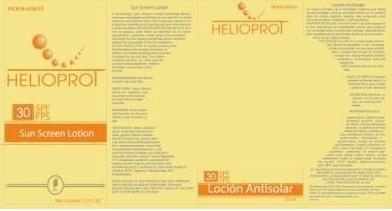 DRUG LABEL: DERMAPROT
NDC: 66854-026 | Form: LOTION
Manufacturer: SPAI-SONS PHARMACEUTICAL INTERNATIONAL COSMETICS
Category: otc | Type: HUMAN OTC DRUG LABEL
Date: 20120607

ACTIVE INGREDIENTS: OCTINOXATE 7.5 mL/100 mL; TITANIUM DIOXIDE 3 mL/100 mL; AVOBENZONE 2.5 mL/100 mL; OXYBENZONE 1.5 mL/100 mL
INACTIVE INGREDIENTS: WATER; PROPYLENE GLYCOL; GLYCERIN; ALUMINUM OXIDE; DIMETHICONE; SILICON DIOXIDE; GLYCERYL MONOSTEARATE; ALOE VERA LEAF; CHAMOMILE; CETYL ALCOHOL; .ALPHA.-TOCOPHEROL ACETATE, D-; OCTYLDODECANOL; DICAPRYLYL CARBONATE; MEDIUM-CHAIN TRIGLYCERIDES; POLYSORBATE 20; CETOSTEARYL ALCOHOL; SODIUM CETOSTEARYL SULFATE; CHAMOMILE FLOWER OIL; EDETATE DISODIUM; METHYLPARABEN; BUTYLATED HYDROXYTOLUENE; PROPYLPARABEN

DERMAPROT HELIOPROT LOCION ANTISOLAR SPF 30

ACTIVE INGREDIENT

ETHYLHEXYL METHOXYCINNAMATE, TITANIUM DIOXIDE, BUTYL METHOXYDIBENZOYLMETHANE, BENZOPHENONE-3, are a set of physical and chemical filters that provide SPF 30

PURPOSE

Sunscreen lotion from wide spectrum sunscreen SPF 30

Keep out of reach of children

INDICATIONS AND USAGE

Provides moderate protection against sun. This product is for topical application.

WARNINGS

Avoid the contact with eyes, rinse with water to remove.

Do not apply this product on under six months aged children

DOSAGE AND ADMINISTRATION

Rub to cover the area to be protected and wait for its full absorption

INACTIVE INGREDIENT

Solar protector UVA UVB has an aqeous base where we deposited all the active ingredients to garantee a wide range of the sun protection; rehydrates the skin tissues maintining cellular bioactivity without the inconvenient of the oily foundations.

IMAGE OF THE CARTON LABEL